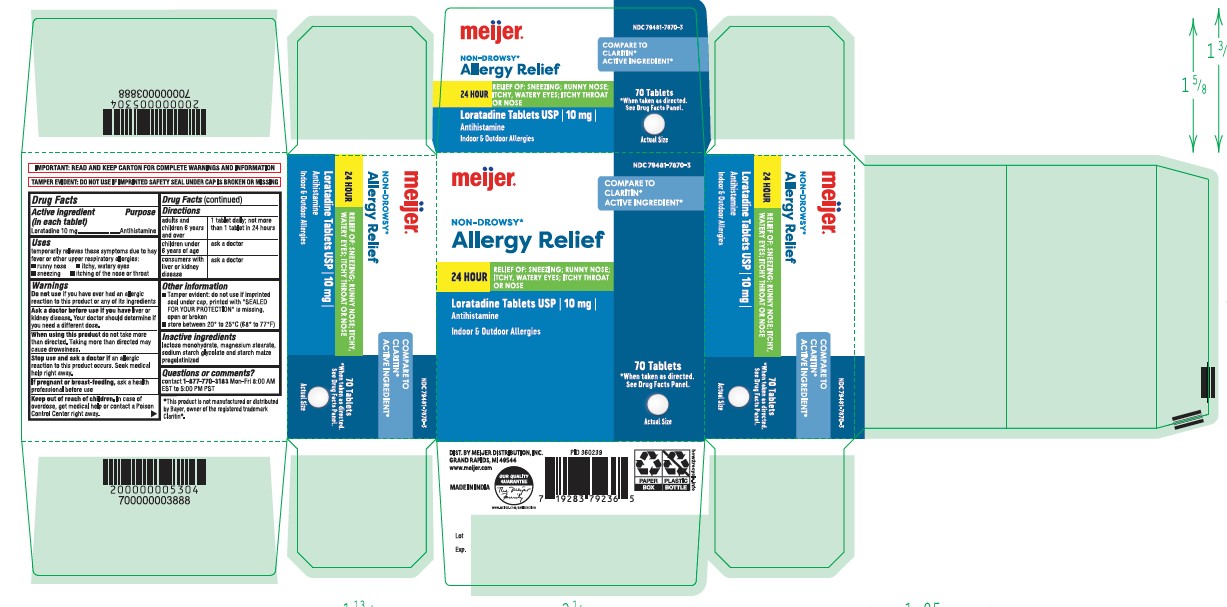 DRUG LABEL: Loratadine 10mg
NDC: 79481-7870 | Form: TABLET
Manufacturer: Meijer
Category: otc | Type: HUMAN OTC DRUG LABEL
Date: 20251219

ACTIVE INGREDIENTS: LORATADINE 10 mg/1 1
INACTIVE INGREDIENTS: MAGNESIUM STEARATE; SODIUM STARCH GLYCOLATE TYPE A POTATO; STARCH, CORN; LACTOSE MONOHYDRATE

Loratadine Tabets 10mg
Antihistamine
INDOOR & OUTDOOR ALLERGIES
Relief of:
Sneezing
Runny Nose
Itchy, Watery Eyes
Itchy Throat or Nose

Active ingredient (in each tablet)

Loratadine 10 mg

Purpose

Antihistamine

Uses

temporarily relieves these symptoms due to hay fever or other upper respiratory allergies:
 runny nose  itchy, watery eyes
 sneezing  itching of the nose or throat

Do not use

if you have ever had an allergic reaction to this product or any of its ingredients

Ask a doctor before use if you have

liver or kidney disease. Your doctor should determine if you need a different dose.

When using this product

do not take more than directed. Taking more than directed may cause drowsiness.

Stop use and ask a doctor if

an allergic reaction to this product occurs. Seek medical help right away.

If pregnant or breast-feeding,

ask a health professional before use

Keep out of reach of children.

In case of overdose, get medical help or contact a Poison Control Center right away.

Directions

adults and 1 tablet daily; not more
than 1 tablet in 24 hours
children 6 years
and over

children under ask a doctor
6 years of age

consumers with ask a doctor
liver or kidney
disease

Other information

 Tamper evident: do not use if imprinted seal under cap, printed with "SEALED FOR YOUR PROTECTION" is missing, open or broken
 store between 20° to 25°C (68° to 77°F)

Inactive ingredients

lactose monohydrate, magnesium stearate, sodium starch glycolate and starch maize pregelatinized

Questions or comments?

contact 1-877-770-3183 Mon-Fri 8:00 AM EST to 5:00 PM PST